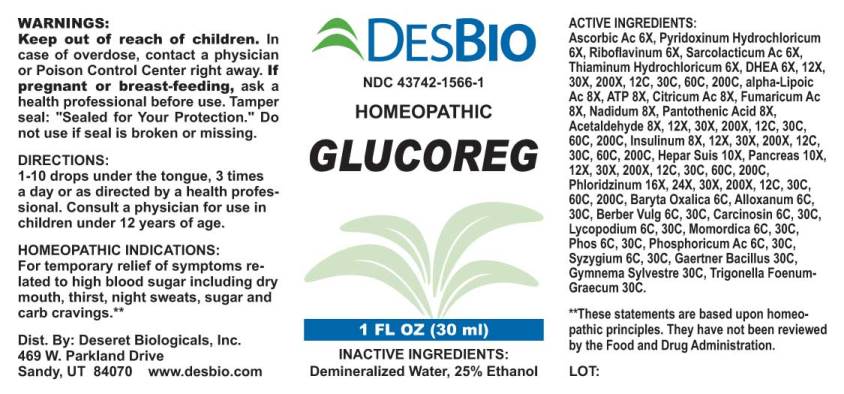 DRUG LABEL: Glucoreg
NDC: 43742-1566 | Form: LIQUID
Manufacturer: Deseret Biologicals, Inc.
Category: homeopathic | Type: HUMAN OTC DRUG LABEL
Date: 20221229

ACTIVE INGREDIENTS: ASCORBIC ACID 6 [hp_X]/1 mL; PYRIDOXINE HYDROCHLORIDE 6 [hp_X]/1 mL; RIBOFLAVIN 6 [hp_X]/1 mL; LACTIC ACID, L- 6 [hp_X]/1 mL; THIAMINE HYDROCHLORIDE 6 [hp_X]/1 mL; PRASTERONE 6 [hp_X]/1 mL; ADENOSINE TRIPHOSPHATE DISODIUM 8 [hp_X]/1 mL; THIOCTIC ACID 8 [hp_X]/1 mL; ANHYDROUS CITRIC ACID 8 [hp_X]/1 mL; FUMARIC ACID 8 [hp_X]/1 mL; NADIDE 8 [hp_X]/1 mL; PANTOTHENIC ACID 8 [hp_X]/1 mL; ACETALDEHYDE 8 [hp_X]/1 mL; INSULIN PORK 8 [hp_X]/1 mL; PORK LIVER 10 [hp_X]/1 mL; SUS SCROFA PANCREAS 10 [hp_X]/1 mL; PHLORIZIN 16 [hp_X]/1 mL; BARIUM OXALATE 6 [hp_C]/1 mL; ALLOXAN 6 [hp_C]/1 mL; BERBERIS VULGARIS ROOT BARK 6 [hp_C]/1 mL; HUMAN BREAST TUMOR CELL 6 [hp_C]/1 mL; LYCOPODIUM CLAVATUM SPORE 6 [hp_C]/1 mL; MOMORDICA BALSAMINA IMMATURE FRUIT 6 [hp_C]/1 mL; PHOSPHORIC ACID 6 [hp_C]/1 mL; PHOSPHORUS 6 [hp_C]/1 mL; SYZYGIUM CUMINI SEED 6 [hp_C]/1 mL; INSULIN HUMAN 12 [hp_C]/1 mL; SALMONELLA ENTERICA SUBSP. ENTERICA SEROVAR ENTERITIDIS 30 [hp_C]/1 mL; GYMNEMA SYLVESTRE LEAF 30 [hp_C]/1 mL; TRIGONELLA FOENUM-GRAECUM WHOLE 30 [hp_C]/1 mL
INACTIVE INGREDIENTS: WATER; ALCOHOL

Drug Facts:

ACTIVE INGREDIENTS:

Ascorbic Acid 6X, Pyridoxinum Hydrochloricum 6X, Riboflavinum 6X, Sarcolacticum Acidum 6X, Thiaminum Hydrochloricum 6X, DHEA (Dehydroepiandrosterone) 6X, 12X, 30X, 200X, 12C, 30C, 60C, 200C, Adenosinum Triphosphoricum Dinatrum 8X, alpha-Lipoicum Acidum 8X, Citricum Acidum 8X, Fumaricum Acidum 8X, Nadidum 8X, Pantothenic Acid 8X, Acetaldehyde 8X, 12X, 30X, 200X, 12C, 30C, 60C, 200C, Insulinum (Suis) 8X, 12X, 30X, 200X, 12C, 30C, 60C, 200C, Insulinum (Human) 12C, 30C, 60C, 200C, Hepar Suis 10X, Pancreas Suis 10X, Phloridzinum 16X, 24X, 30X, 200X, 12C, 30C, 60C, 200C, Baryta Oxalica 6C, Alloxanum 6C, 30C, Berberis Vulgaris 6C, 30C, Carcinosin 6C, 30C, Lycopodium Clavatum 6C, 30C, Momordica Balsamina 6C, 30C, Phosphoricum Acidum 6C, 30C, Phosphorus 6C, 30C, Syzygium Jambolanum 6C, 30C, Gaertner Bacillus (Bach) 30C, Gymnema Sylvestre 30C, Trigonella Foenum-Graecum 30C.

HOMEOPATHIC INDICATIONS:

For temporary relief of symptoms related to high blood sugar including dry mouth, thirst, night sweats, sugar and carb cravings.**

**These statements are based upon traditional homeopathic principles. They have not been reviewed by the Food and Drug Administration.

WARNINGS:

Keep out of reach of children. In case of overdose, contact physician or a Poison Control Center right away.

If pregnant or breast-feeding, ask a health professional before use.

Tamper seal: "Sealed for Your Protection." Do not use if seal is broken or missing.

Keep out of reach of children. In case of overdose, contact physician or a Poison Control Center right away.

DIRECTIONS:

1-10 drops under the tongue, 3 times a day or as directed by a health professional. Consult a physician for use in children under 12 years of age.

HOMEOPATHIC INDICATIONS:

For temporary relief of symptoms related to high blood sugar including dry mouth, thirst, night sweats, sugar and carb cravings.**

**These statements are based upon traditional homeopathic principles. They have not been reviewed by the Food and Drug Administration.

INACTIVE INGREDIENTS:

Demineralized Water, 25% Ethanol

QUESTIONS:

Dist. By: Deseret Biologicals, Inc.
469 W. Parkland Drive
Sandy, UT 84070 www.desbio.com

PACKAGE LABEL DISPLAY:

DESBIO
NDC 43742-1566-1
HOMEOPATHIC
GLUCOREG
1 FL OZ (30 ml)